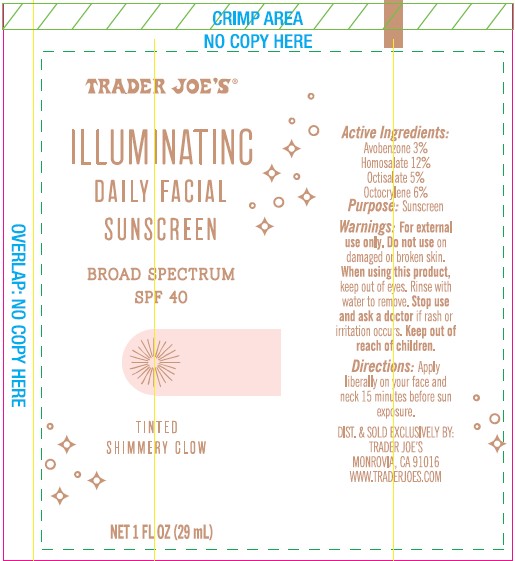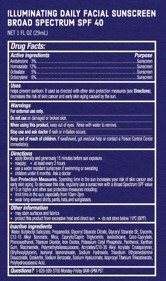 DRUG LABEL: TRADER JOES ILLUMINATING DAILY FACIAL SUNSCREEN

NDC: 71270-157 | Form: LOTION
Manufacturer: Trader Joe's Company
Category: otc | Type: HUMAN OTC DRUG LABEL
Date: 20241022

ACTIVE INGREDIENTS: AVOBENZONE 3 g/100 mL; HOMOSALATE 12 g/100 mL; OCTISALATE 5 g/100 mL; OCTOCRYLENE 6 g/100 mL
INACTIVE INGREDIENTS: XANTHAN GUM; TITANIUM DIOXIDE; FERRIC OXIDE RED; POLYMETHYLSILSESQUIOXANE (4.5 MICRONS); ISONONYL ISONONANOATE; ALKYL (C12-15) BENZOATE; MICA; ISODODECANE; COCO-CAPRYLATE; PANTHENOL; ACRYLATES/C10-30 ALKYL ACRYLATE CROSSPOLYMER (60000 MPA.S); TRISODIUM ETHYLENEDIAMINE DISUCCINATE; CERESIN; GLYCERIN; BUTYLOCTYL SALICYLATE; PROPANEDIOL; GLYCERYL STEARATE CITRATE; PHENOXYETHANOL; GLYCERYL STEARATE SE; ETHYLHEXYLGLYCERIN; SODIUM BENZOATE; SODIUM HYDROXIDE; POLYHYDROXYSTEARIC ACID (2300 MW); HYALURONATE SODIUM; ISOPROPYL TITANIUM TRIISOSTEARATE; WATER; MEDIUM-CHAIN TRIGLYCERIDES; POTASSIUM CETYL PHOSPHATE; NIACINAMIDE

TRADER JOE’S (as PLD) - ILLUMINATING DAILY FACIAL SUNSCREEN BROAD SPECTRUM SPF 40 (71270-157)

ACTIVE INGREDIENT

AVOBENZONE 3%

HOMOSALATE 12%

OCTISALATE 5%

OCTOCRYLENE 6%

PURPOSE

SUNSCREEN

USES

- HELPS PREVENT SUNSCREEN
- IF USED AS DIRECTED WITH OTHER SUN PROTECTION MEASURES (SEE DIRECTIONS), DECREASES THE RISK OF SKIN CANCER AND EARLY SKIN AGING CAUSED BY THE SUN.

WARNINGS

For external use only.

Do not useon damaged or broken skin.

When using this product, keep out of eyes. Rinse with water to remove.

Stop use and ask a doctorif rash occurs.

Keep out of reach of children.If swallowed, get medical help or contact a Poison Control Center immediately.

DIRECTIONS

- Apply liberally to face and body 15 minutes before sun exposure.
- Reapply: after 80 minutes of swimming or sweating
- immediately after towel drying
- at least every 2 hours.
- Children under 6 months: ask a doctor.

Sun Protection Measures.Spending time in the sun increases your risk of skin cancer and early skin aging. To decrease this risk, regularly use a sunscreen with a Broad Spectrum SPF 15 value or higher along with other sun protection measures including:

- limit time in the sun, especially from 10 a.m. – 2 p.m.
- wear long sleeved shirts, pants, hats and sunglasses.

OTHER INFORMATION

- Protect the product in this container from excessive heat and direct sun
- May stain surfaces and fabrics.

INACTIVE INGREDIENTS

WATER (AQUA), BUTYLOCTYL SALICYLATE, PROPANEDIOL, GLYCERYL STEARATE CITRATE, GLYCERYL STEARATE SE, GLYCERIN, C12-15 ALKYL BENZOATE, MICA, CAPRYLIC/CAPRIC TRIGLYCERIDE, ISODODECANE, COCO-CAPRYLATE, PHENOXYETHANOL, POTASSIUM CETYL PHOSPHATE, PANTHENOL, XANTHAN GUM, NIACINAMIDE, POLYMETHYLSILSESQUIOXANE, ACRYLATES/C10-30 ACRYLATE COPOLYMER, ETHYLHEXYLGLYCERIN, ISONONYL ISONONOATE, SODIUM HYDROXIDE, TRISODIUM ETHYLENEDIAMINE DISUCCINATE, OZOKERITE, SODIUM BENZOATE, SODIUM HYALURONATE, ISOPROPYL TITANIUM DIISOSTEARATE, POLYHYDROXYSTEARIC ACID, TITANIUM DIOXIDE, IRON OXIDES.

QUESTIONS OR COMMENTS?

1- 626-599-3700Monday – Friday 9 AM – 5 PM PST